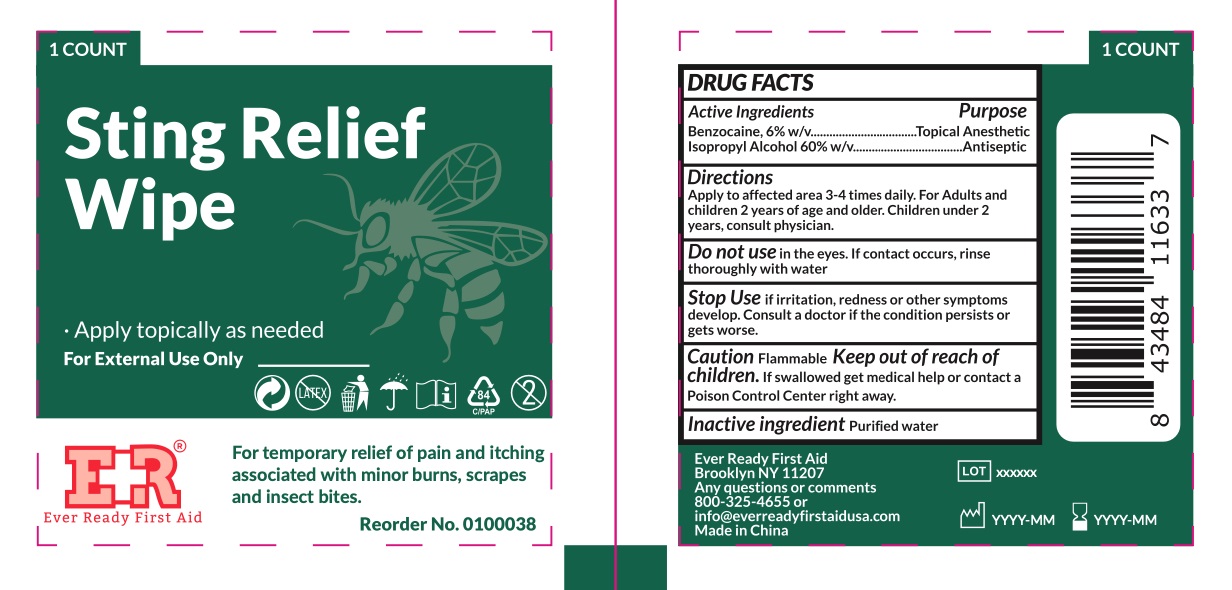 DRUG LABEL: Sting Relief Wipe
NDC: 72976-010 | Form: SWAB
Manufacturer: EVER READY FIRST AID
Category: otc | Type: HUMAN OTC DRUG LABEL
Date: 20230201

ACTIVE INGREDIENTS: ISOPROPYL ALCOHOL 600 mg/1 mL; BENZOCAINE 60 mg/1 mL
INACTIVE INGREDIENTS: WATER

Ever Ready First Aid Sting Relief Wipe

Active Ingredients

Benzocaine 6% w/v

Isopropyl Alcohol 60% w/v

Purpose

Topical Anesthetic

Antiseptic

INDICATIONS AND USAGE

For temporary relief of pain and itching associated with minor burns, scrapes and insect bites.

Warnings

For External Use Only

CautionFlammable

Do not use

in the eyes. If contact occurs, rinse thoroughly with water

Stop Use

If irritation, redness or other symptoms develop. Consult a doctor if the condition persists or gets worse.

Keep out of reach of children.

If swallowed get medical help or contact a Poison Control Center right away.

Directions

Apply to affected area 3-4 times daily. For adults and children 2 years of age and older. Children under 2 years, consult physician.

Inactive ingredient

Purified water